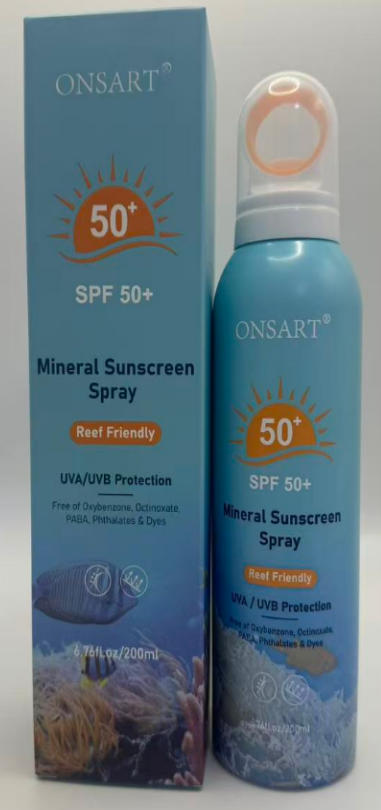 DRUG LABEL: ONSART Mineral Sunscreen
NDC: 87204-159 | Form: SPRAY
Manufacturer: Guangzhou Huixue Biotechnology Co., Ltd.
Category: otc | Type: HUMAN OTC DRUG LABEL
Date: 20260119

ACTIVE INGREDIENTS: ZINC OXIDE 48 mg/200 g
INACTIVE INGREDIENTS: CITRONELLOL; GERANIOL; BENZYL BENZOATE; LINALYL ACETATE; MENTHOL; AQUA; BENZYL ALCOHOL; HEXYL CINNAMAL; ALPHA-ISOMETHYL IONONE; LINALOOL; GERANYL ACETATE; POGOSTEMON CABLIN OIL; ACETYL CEDRENE; AMYL SALICYLATE; PELARGONIUM GRAVEOLENS FLOWER OIL; COUMARIN

ACTIVE INGREDIENT

Zinc Oxide 24%

INACTIVE INGREDIENT

ALOE BARBADENSIS LEAF JUICE, DIBUTYL ADIPATE, ISOOCTANE, LAURYL PEG-10 TRIS(TRIMETHYLSILOXY)SILYLETHYL DIMETHICONE, POLYHYDROXYSTEARIC ACID, DECYL GLUCOSIDE, PHENOXYETHANOL, TOCOPHEROL, BISABOLOL, SILICA, BUTYLENE GLYCOL, ETHYLHEXYLGLYCERIN, DIPOTASSIUM GLYCYRRHIZATE, STEARIC ACID, PROPYLENE GLYCOL, XANTHAN GUM, OPUNTIA DILLENII EXTRACT, OPHIOPOGON JAPONICUS ROOT EXTRACT, AVENA SATIVA BRAN EXTRACT, PAEONIA ALBIFLORA ROOT EXTRACT, SCUTELLARIA BAICALENSIS ROOT EXTRACT, GREEN TEA （CAMELLIA SINENSIS）EXTRACT, WATER, HYALURONIC ACID, CAPRYLYL GLYCOL, ISOBUTANE, TOCOPHERYL ACETATE.

PURPOSE

unscreen

INDICATIONS AND USAGE

Uses Helps prevent sunburm. .l used as directed with other sun protection measures (see Directlens), decreases the risk of skin cancer and early skin aging caused by the sun.

WARNINGS

Warnings For enternal use only, - Danger. Flammable. Contents under pres - De not use near fire, heat or while smoking. Do not puncture or incinerate. Store at temperatures below 120*F (48C). - De not wse on damaged or braken skin. - When using this product, keep ouf of eyes. If contact occurs, rinse thoroughly with waler. . Stop use and aak a doctor if rash occurs. + Koop out of reach of chiidren. If swailowed, get medical help or contact a Poison Contrel Center iright away. - Usn only as directed. Intentional misuse by deliberately concentrating and inhaling the comtents can be harmful or fatal.

KEEP OUT OF REACH OF CHILDREN

If swallowed, get medical help or contact a Poison Control Center right away.

WHEN USING

Directions - Shake well before sach use. Spray liberally and spread evenly by hand 15 minules before sun exppsure. • Hald contsiner 4 tp & inches from the skin to apply.Rub in. -Do not apply in windy conditions. Use in a well-vent lated area. Reapply: Atter BD minutes of swimming. sweating .or immediately after towel drying A! leust every 2 hours. . Sun Protaction Measures: Spending time in the sun incresses your risk of skin cancer and early skin aging. To decrease this risk, reggularty use a sunscreen with a Biroed Spectrum SPF velue of 15 or higher and other sun protection measures includirg: - Limil time in the sun, especially from 10 am-2 pm. -Wsar long-slesve shiris, pands, hats, and Snglascs. Children under é months: Ask a doctor

STOP USE

Chest pain, rapid heart beat, faintness, or dizziness occurs sudden, unexplained weight gain occurs,your hands or feet swell.

DO NOT USE

You ae under 18 years of age, Do not use it on babies and children your scalp is red.inflamed.infected, irritated, or painful
You use other medicines on the scalp.Ask a doctor before use if you hace heart disease..

DOSAGE AND ADMINISTRATION

Twice each day,4 sprays (1ml)each time. 50 days supply